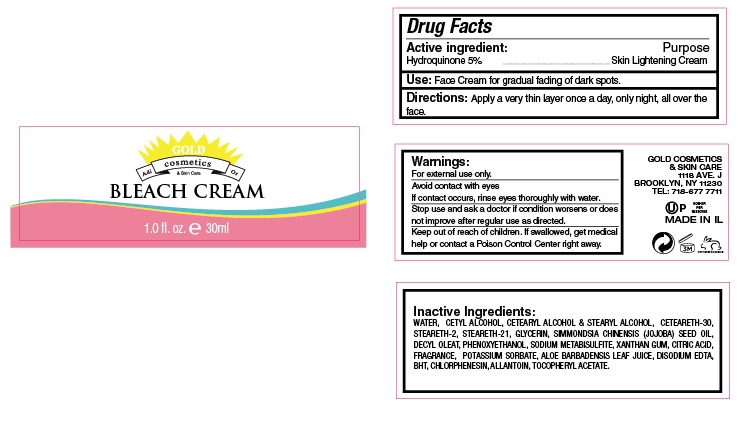 DRUG LABEL: Gold Cosmetics Bleach Cream
NDC: 69435-1702 | Form: CREAM
Manufacturer: Peer Pharm Ltd
Category: otc | Type: HUMAN OTC DRUG LABEL
Date: 20171116

ACTIVE INGREDIENTS: HYDROQUINONE 100 mg/5 mg
INACTIVE INGREDIENTS: GLYCERIN; JOJOBA OIL; DECYL OLEATE; SODIUM DITHIONATE; XANTHAN GUM; PHENOXYETHANOL; CITRIC ACID MONOHYDRATE; POTASSIUM SORBATE; ALOE VERA LEAF; BUTYLATED HYDROXYTOLUENE; CETEARETH-30; WATER; CETOSTEARYL ALCOHOL; STEARYL ALCOHOL; CHLORPHENESIN; STEARETH-21; STEARETH-2; EDETATE DISODIUM ANHYDROUS; ALPHA-TOCOPHEROL ACETATE; CETYL ALCOHOL; ALLANTOIN

Bleach Cream

ACTIVE INGREDIENT

Hydroquinone 5%

PURPOSE

Face cream for gradual fading of dark spots

INDICATIONS AND USAGE

Face cream for gradual fading of dark spots

Apply a very thin layer once a day, only at night, all over the face

DOSAGE AND ADMINISTRATION

Apply a very thin layer once a day, only at night, all over the face

Warnings:

- For external use only
- Avoid contact with eyes
- If contact occurs, rinse eyes thoroughly with water

Keep out of reach of children